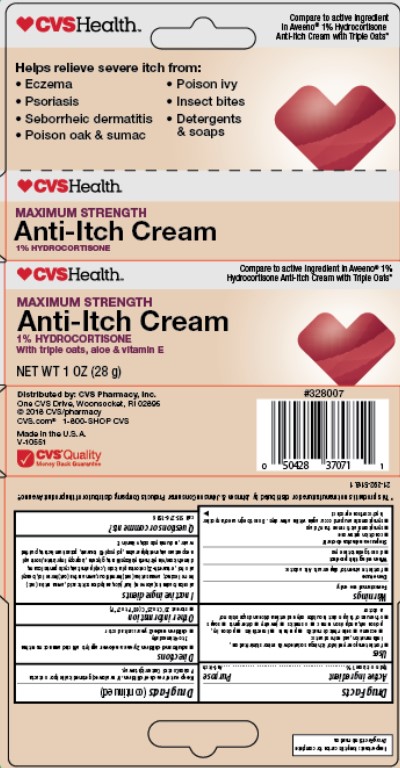 DRUG LABEL: CVS Anti itch
NDC: 69842-292 | Form: CREAM
Manufacturer: CVS
Category: otc | Type: HUMAN OTC DRUG LABEL
Date: 20241213

ACTIVE INGREDIENTS: HYDROCORTISONE 1 g/100 g
INACTIVE INGREDIENTS: GLYCERIN; ALOE VERA LEAF; METHYLPARABEN; CETOSTEARYL ALCOHOL; WATER; .ALPHA.-TOCOPHEROL ACETATE; ISOPROPYL MYRISTATE; POTASSIUM LACTATE; CYCLOMETHICONE 5; VINYLTRIMETHYLSILYLOXY SILICATE; SODIUM HYDROXIDE; ANHYDROUS CITRIC ACID; PEG-40 STEARATE; CETYL PALMITATE; OAT KERNEL OIL; DIMETHICONE; ISOSTEARYL NEOPENTANOATE; BENZYL ALCOHOL

CVS Hydrocortisone with oats

Active Ingredient

Hydrocortisone 1 %

Uses

for the temporary relief of itching associated with minor skin irritations, inflammation, and rashes due to:

eczema

seborrheic dermatitis

psoriasis

insect bites

poison ivy, poison oak, and poison sumac

cosmetics

jewelry

detergents

soaps

temporarily relieves external anal and genital itching

other uses of this product should be only under the advice and supervision of a doctor

Warnings

For external use only

When using this product

do not get into the eyes

Do not use

for the treatment of diaper rash. Ask a doctor.

Stop us and ask doctor if

condition gets worse, or if symptoms last for more than 7 days or clear up and occur again within a few days. Do not begin use of any other hydrocortisone product.

Keep out of reach of children

If swallowed, get medical help or contact a Poison Control Center right away.

Directions

adults and children 2 years and over: apply to affected area not more than 3 to 4 times daily

children under 2 years: ask a doctor

Other information

store at 20 °C to 25 °C (68 °F to 77 °F)

Inactive ingredient

aloe barbadensis (aloe vera) leaf juice, anhydrous citric acid, avena sativa (oat) kernel extract, avena sativa (oat) kernel flour, avena sativa (oat) kernel oil, benzyl alcohol, ceteareth-20, cetostearyl alcohol, cetyl palmitate, cyclopentasiloxane, dimethicone/vinyltrimethylsiloxysilicate, glycerin, isopropyl myristate, isostearyl neopentanoate, methylparaben,
polyoxyl 40 stearate, potassium lactate, purified water, sodium hydroxide, vitamin E

Purpose

Anti-Itch